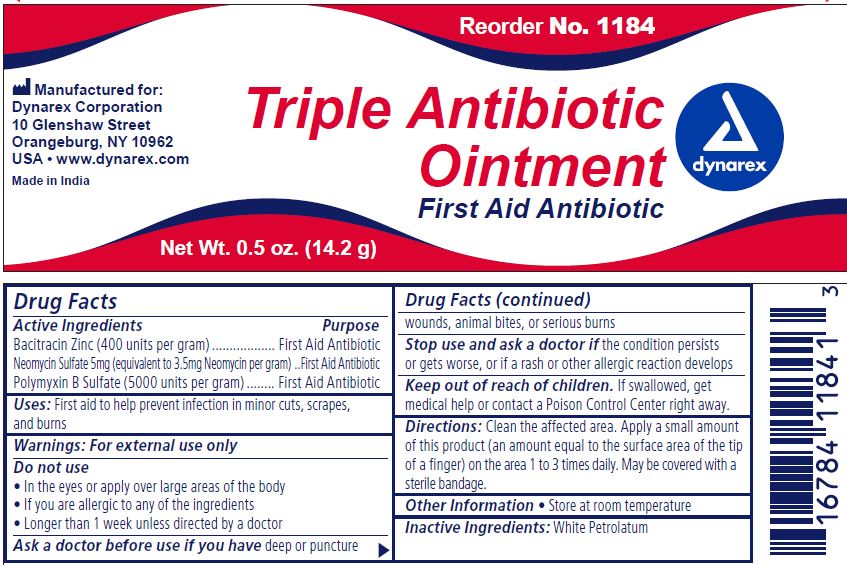 DRUG LABEL: Triple Antibiotic
NDC: 67777-118 | Form: OINTMENT
Manufacturer: Dynarex Corporation
Category: otc | Type: HUMAN OTC DRUG LABEL
Date: 20190207

ACTIVE INGREDIENTS: BACITRACIN ZINC 400 1/1000 mg; NEOMYCIN SULFATE 3.5 mg/1000 mg; POLYMYXIN B SULFATE 5000 1/1000 mg
INACTIVE INGREDIENTS: PETROLATUM

1184 Triple Antibiotic NDC 67777-118-40

Active Ingredients

Bacitracin Zinc (400 units per gram)

Neomycin Sulfate 5mg (equivalent to 3.5mg Neomycin per gram)

Polymyxin B Sulfate (5000 units per gram)

Purpose

First Aid Antibiotics

Uses:

First aid to help prevent infection in minor cuts, scrapes, and burns

Warnings:

For external use only

Do not use

- In the eyes or apply over large areas of the body
- If you are allergic to any of the ingredients
- Longer than 1 week unless directed by a doctor

Ask a doctor before use if you have

deep or puncture wounds, animal bites, or serious burns

Stop use and ask a doctor if

the condition persists or gets worse, or if a rash or other allergic reaction develops

KEEP OUT OF REACH OF CHILDREN

If swallowed, get medical help or contact a Poison Control Center right away.

Directions

Clean the affected area. Apply a small amount of this product (an amount equal to the surface area of the tip of a finger) on the area 1 to 3 times daily. May be covered with a sterile bandage.

Other Information

Store at room temperature.

Inactive Ingredient

White Petrolatum